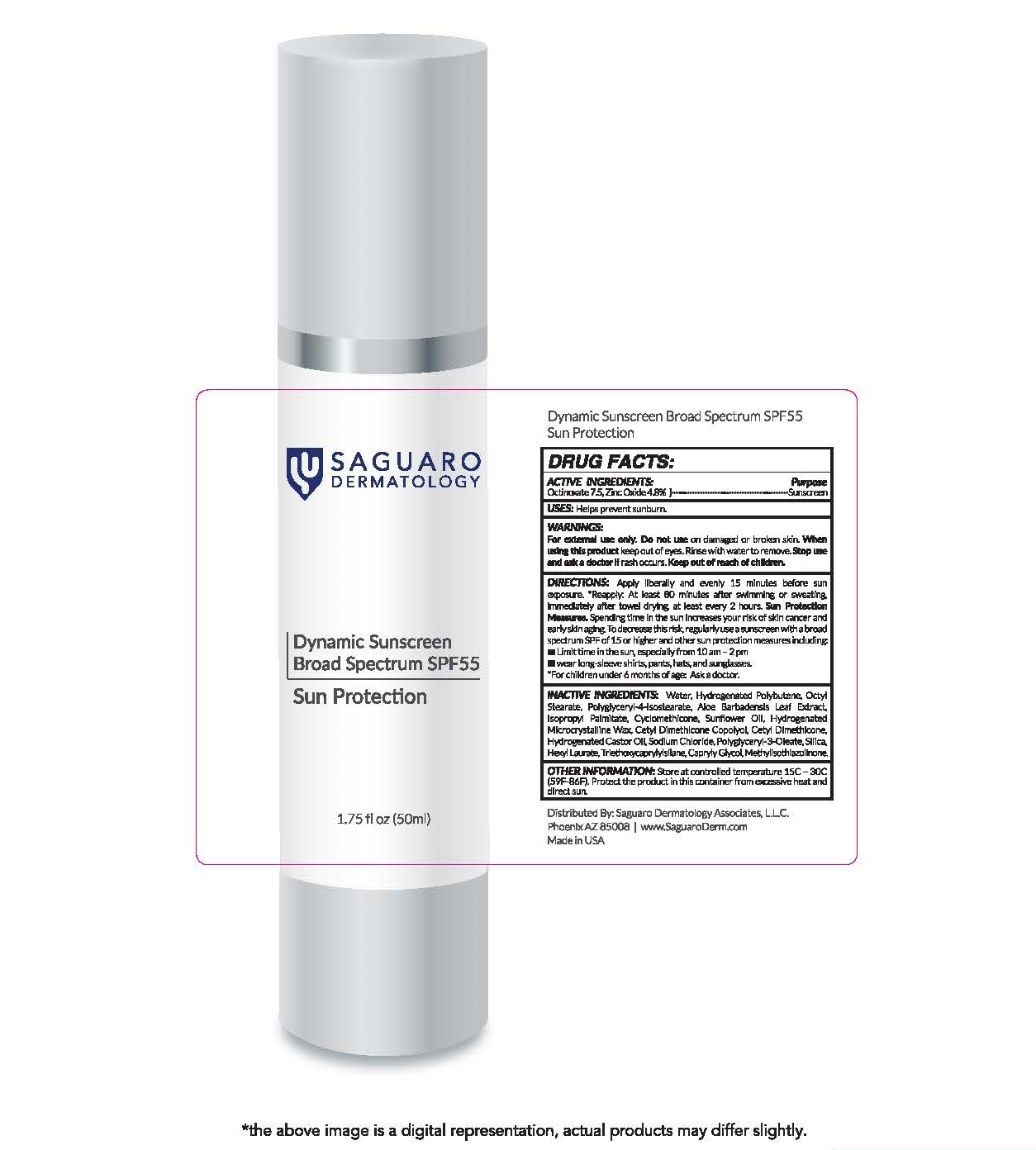 DRUG LABEL: Dynamic Sunscreen Broad Spectrum SPF 55 Sun Protection
NDC: 82365-5550 | Form: CREAM
Manufacturer: Saguaro Dermatology Associates, L.L.C.
Category: otc | Type: HUMAN OTC DRUG LABEL
Date: 20240116

ACTIVE INGREDIENTS: OCTINOXATE 75 mg/1 g; ZINC OXIDE 48 mg/1 g
INACTIVE INGREDIENTS: PHENOXYETHANOL; WATER; ISOCETYL STEARATE; SORBITOL; CETOSTEARYL ALCOHOL; CYCLOMETHICONE 5; GLYCERYL MONOSTEARATE; PEG-100 STEARATE; ALCOHOL; OCTISALATE; POLYOXYL 20 CETOSTEARYL ETHER; .ALPHA.-TOCOPHEROL ACETATE; VINYLPYRROLIDONE/EICOSENE COPOLYMER; HYDROXYETHYL ACRYLATE/SODIUM ACRYLOYLDIMETHYL TAURATE COPOLYMER (100000 MPA.S AT 1.5%); ETHYLHEXYLGLYCERIN; BETULA PUBESCENS BARK; GARDEN CRESS SPROUT; SAGE; COLA ACUMINATA SEED; CAMELLIA OLEIFERA LEAF; ALOE VERA LEAF; XANTHAN GUM; ISOMALT; EDETATE DISODIUM ANHYDROUS; TRIETHOXYCAPRYLYLSILANE; SODIUM BENZOATE; CAPRYLYL GLYCOL

Dynamic Sunscreen Broad Spectrum SPF 55 Sun Protection

DRUG FACTS

ACTIVE INGREDIENTS

Octinoxate 7.5%

Zinc Oxide 4.8%

PURPOSE

Sunscreen

USES

Help prevent sunburn.

WARNINGS

For external use only.

Do not use on damaged or broken skin.

When using this product keep out of eyes. Rinse with water to remove.

Stop use and ask a doctor if rash or irritation occurs.

Keep out of reach of children. If product is swallowed, get medical help or contact a Poison Control Center right away.

DIRECTIONS

Apply liberally and evenly 15 minutes before sun exposure. [For children under 6 months of age: Ask a doctor.] Reapply:

At least 80 minutes after swimming or sweating, immediately after towel drying, at least every 2 hours.

- Sun Protection Measures. Spending time in the sun increases your risk of skin cancer and early skin aging. To decrease this risk, regularly use a sunscreen with a broad spectrum SPF of 15 or higher and other sun protection measures including:
- limit time in the sun, especially from 10 a.m. – 2 p.m.
- wear long-sleeve shirts, pants, hats, and sunglasses.

INACTIVE INGREDIENTS

Water, Hydrogenated Polybutene, Octyl Stearate, Polyglyceryl-4-Isostearate, Aloe Barbadensis Leaf Extract, Isopropyl Palmitate, Cyclomethicone, Sunflower Oil, Hydrogenated Microcrystalline Wax, Cetyl Dimethicone Copolyol, Cetyl Dimethicone, Hydrogenated Castor Oil, Sodium Chloride, Polyglyceryl-3-Oleate, Silica, Hexyl Laurate, Triethoxycaprylylsilane, Capryly Glycol, Methylisothiazolinone.

OTHER INFORMATION

Store at controlled temperature 15C – 30C (59F-86F). Protect the product in this container from excessive heat and direct sun.

Saguaro Dermatology Dynamic Sunscreen Broad Spectrum SPF 55 Sun Protection 1.75 fl oz (50ml)

Saguaro Dermatology
Dynamic Sunscreen Broad Spectrum SPF 55
Sun Protection
1.75 fl oz (50ml)